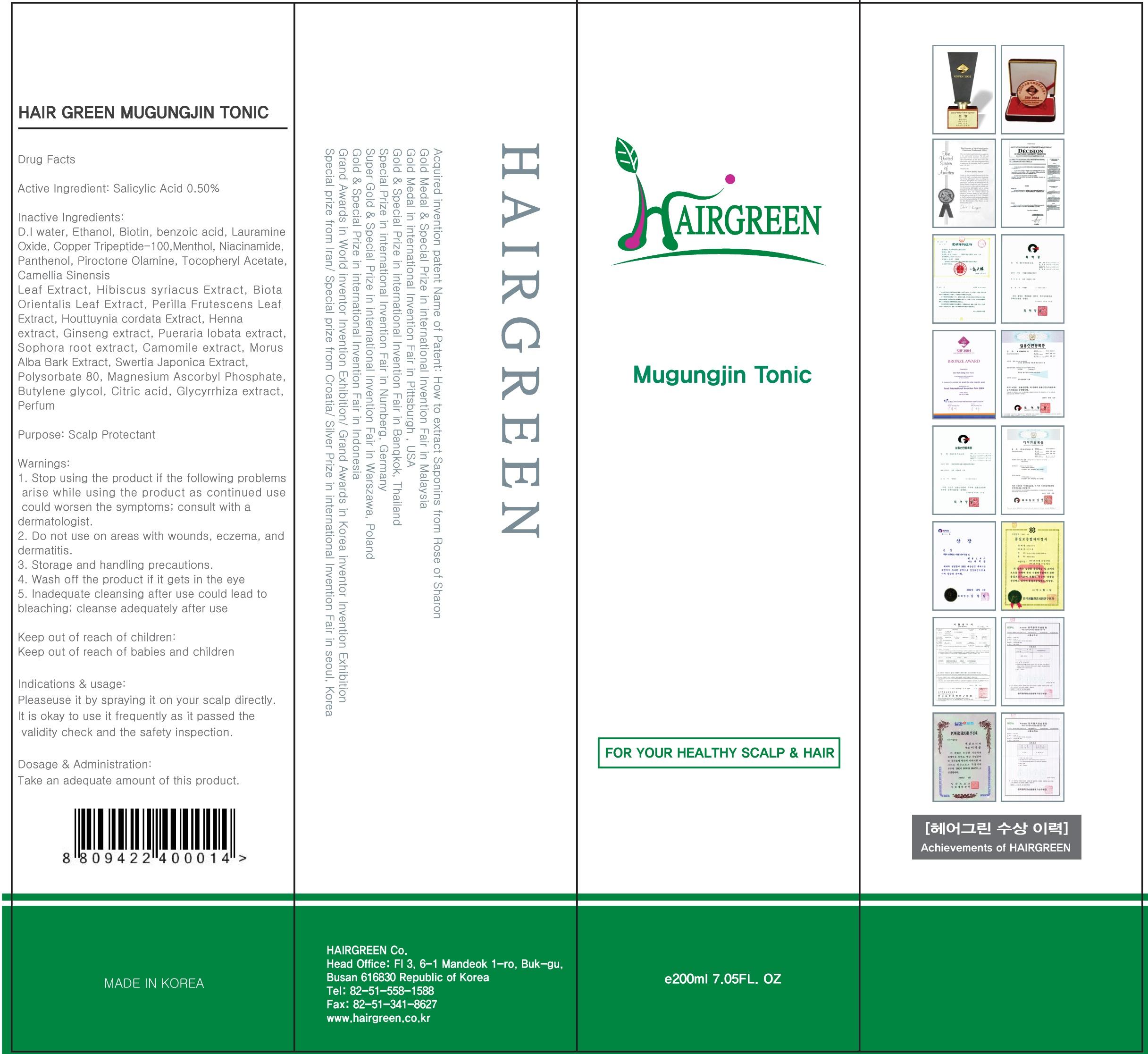 DRUG LABEL: Hair Green Mugungjin Tonic
NDC: 69773-020 | Form: SOLUTION
Manufacturer: HAIRGREEN
Category: otc | Type: HUMAN OTC DRUG LABEL
Date: 20150923

ACTIVE INGREDIENTS: Salicylic Acid 1.0 mg/200 mL
INACTIVE INGREDIENTS: water; Biotin

ACTIVE INGREDIENT

Active Ingredient: Salicylic Acid 0.50%

INACTIVE INGREDIENT

Inactive Ingredients: D.I water, Ethanol, Biotin, benzoic acid, Lauramine Oxide, Copper Tripeptide-100, Menthol, Niacinamide, Panthenol, Piroctone Olamine, Tocopheryl Acetate, Camellia Sinensis Leaf Extract, Hibiscus syriacus Extract, Biota Orientalis Leaf Extract, Perilla Frutescens Leaf Extract, Houttuynia cordata Extract, Henna extract, Ginseng extract, Pueraria lobata extract, Sophora root extract, Camomile extract, Morus Alba Bark Extract, Swertia Japonica Extract, Polysorbate 80, Magnesium Ascorbyl Phosphate, Butylene glycol, Citric acid, Glycyrrhiza extract, Perfum

PURPOSE

Purpose: Scalp Protectant

WARNINGS

Warnings: 1. Stop using the product if the following problems arise while using the product as continued use could worsen the symptoms; consult with a dermatologist. 2. Do not use on areas with wounds, eczema, and dermatitis. 3. Storage and handling precautions. 4. Wash off the product if it gets in the eye 5. Inadequate cleansing after use could lead to bleaching; cleanse adequately after use

Keep out of reach of children: Keep out of reach of babies and children

INDICATIONS & USAGE

Indications & usage: Please use it by spraying it on your scalp directly. It is okay to use it frequently as it passed the validity check and the safety inspection.

DOSAGE & ADMINISTRATION

Dosage & Administration: Take an adequate amount of this product.